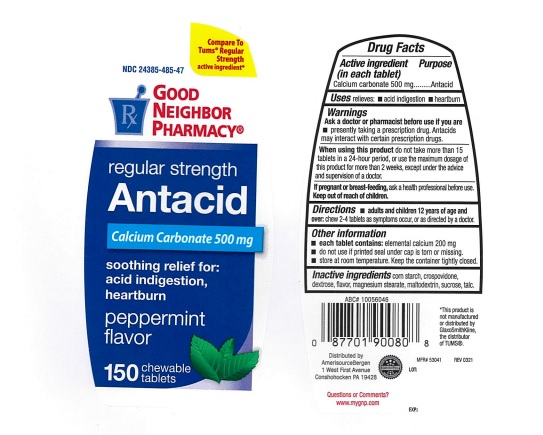 DRUG LABEL: Good Neighbor Pharmacy Antacid
NDC: 24385-485 | Form: TABLET, CHEWABLE
Manufacturer: AmerisourceBergen Drug Corporation
Category: otc | Type: HUMAN OTC DRUG LABEL
Date: 20240709

ACTIVE INGREDIENTS: CALCIUM CARBONATE 500 mg/1 1
INACTIVE INGREDIENTS: STARCH, CORN; CROSPOVIDONE; DEXTROSE, UNSPECIFIED FORM; MAGNESIUM STEARATE; MALTODEXTRIN; SUCROSE; TALC

Good Neighbor Pharmacy Antacid

Drug Facts

Active ingredient (in each tablet)

Calcium carbonate 500 mg

Purpose

Antacid

Uses

- relieves
- acid indigestion
- heartburn

Warnings

Ask a doctor or pharmacist before use if you are

- presently taking a prescription drug. Antacids may interact with certain prescription drugs.

When using this product

do not take more than 15 tablets in a 24-hour period, or use the maximum dosage of this product for more than 2 weeks, except under the advice and supervision of a doctor.

If pregnant or breast feeding,

ask a health professional before use. Keep out of reach of children.

Directions

- adults and children 12 years of age and over: chew 2-4 tablets as symptoms occur, or as directed by a doctor.

Other information

- each tablet contains: elemental calcium 200mg
- do not use if printed seal under cap is torn or missing.
- store at room temperature. keep the container tightly closed.

Inactive ingredients

corn starch, crospovidone, dextrose, flavor, magnesium stearate, maltodextrin, sucrose, talc.

Good Neighbor Pharmacy Antacid

Compare To Tums® Regular Strength active ingredient*

NDC 24385-485-47

GOOD NEIGHBOR PHARMACY

regular strength

Antacid

Calcium Carbonate 500 mg

soothing relief for:

acid indigestion,

heartburn

peppermint flavor

150 chewable tablets